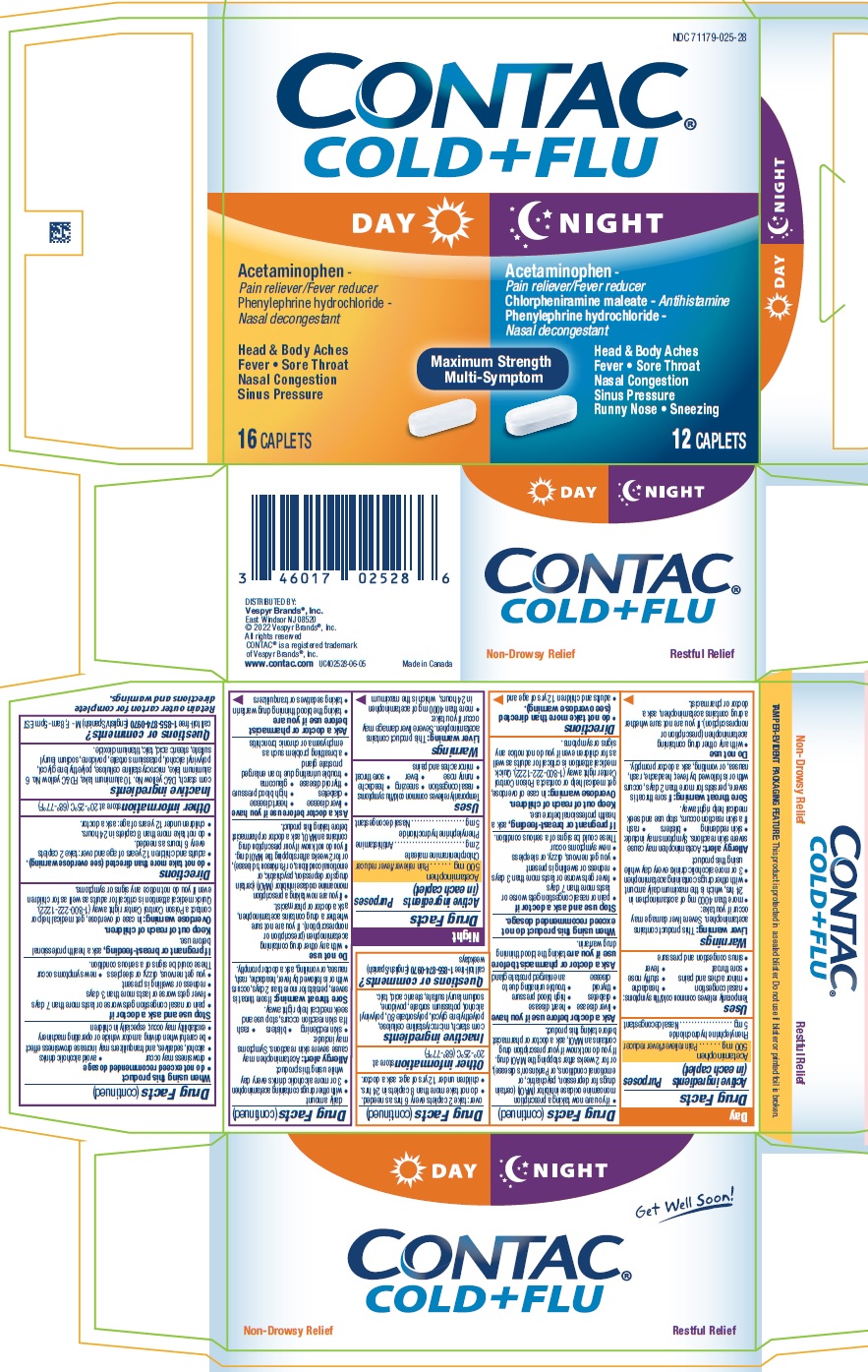 DRUG LABEL: CONTAC
NDC: 71179-025 | Form: KIT | Route: ORAL
Manufacturer: Vespyr Brands, Inc.
Category: otc | Type: HUMAN OTC DRUG LABEL
Date: 20240101

ACTIVE INGREDIENTS: ACETAMINOPHEN 500 mg/1 1; PHENYLEPHRINE HYDROCHLORIDE 5 mg/1 1; PHENYLEPHRINE HYDROCHLORIDE 5 mg/1 1; ACETAMINOPHEN 500 mg/1 1; CHLORPHENIRAMINE MALEATE 2 mg/1 1
INACTIVE INGREDIENTS: STEARIC ACID; POLYETHYLENE GLYCOL, UNSPECIFIED; MICROCRYSTALLINE CELLULOSE; POVIDONE; POTASSIUM SORBATE; STARCH, CORN; POLYSORBATE 80; TALC; POLYVINYL ALCOHOL, UNSPECIFIED; SODIUM LAURYL SULFATE; SODIUM LAURYL SULFATE; D&C YELLOW NO. 10 ALUMINUM LAKE; POLYVINYL ALCOHOL, UNSPECIFIED; STEARIC ACID; MICROCRYSTALLINE CELLULOSE; POTASSIUM SORBATE; TALC; FD&C YELLOW NO. 6; POLYETHYLENE GLYCOL, UNSPECIFIED; STARCH, CORN; POVIDONE; TITANIUM DIOXIDE

CONTAC Cold + Flu Day Night

Active ingredients (in each caplet) (Day)

Acetaminophen 500 mg
Phenylephrine hydrochloride 5 mg

Purposes (Day)

Pain reliever/fever reducer
Nasal decongestant

Uses (Day)

Temporarily relieves common cold/flu symptoms:
• nasal congestion • headache
• minor aches and pains • stuffy nose
• sore throat • fever
• sinus congestion and pressure

Warnings (Day)

Liver warning: This product contains acetaminophen. Severe liver damage may occur if you take:
• more than 4000 mg of acetaminophen in 24 hrs, which is the maximum daily amount
• with other drugs containing acetaminophen
• 3 or more alcoholic drinks every day while using this product
Allergy alert: Acetaminophen may cause severe skin reactions. Symptoms may include:
• skin reddening • blisters • rash
If a skin reaction occurs, stop use and seek medical help right away.
Sore throat warning: If sore throat is severe, persists for more than 2 days, occurs with or is followed by fever, headache, rash, nausea, or vomiting, ask a doctor promptly.

Do not use
• with any other drug containing acetaminophen (prescription or nonprescription). If you are not sure whether a drug contains acetaminophen, ask a doctor or pharmacist.

• if you are now taking a prescription monoamine oxidase inhibitor (MAOI) (certain drugs for depression, psychiatric, or emotional conditions, or Parkinson’s disease), or for 2 weeks after stopping the MAOI drug. If you do not know if your prescription drug contains an MAOI, ask a doctor or pharmacist before taking this product.

Ask a doctor before use if you have
• liver disease • heart disease
• diabetes • high blood pressure
• thyroid • trouble urinating due to disease an enlarged prostate gland

Ask a doctor or pharmacist before use if you are taking the blood thinning drug warfarin.

When using this product do not exceed recommended dosage.

Stop use and ask a doctor if
• pain or nasal congestion gets worse or lasts more than 7 days
• fever gets worse or lasts more than 3 days
• redness or swelling is present
• you get nervous, dizzy, or sleepless
• new symptoms occur

These could be signs of a serious condition.

PREGNANCY OR BREAST FEEDING

If pregnant or breast-feeding, ask a health professional before use.

Keep out of reach of children.
Overdose warning: In case of overdose, get medical help or contact a Poison Control Center right away (1-800-222-1222). Quick
medical attention is critical for adults as well as for children even if you do not notice any signs or symptoms.

Directions (Day)

• do not take more than directed (see overdose warning).
• adults and children 12 yrs of age and over: take 2 caplets every 6 hrs as needed.
• do not take more than 8 caplets in 24 hrs.
• children under 12 yrs of age: ask a doctor.

Other information (Day)

store at 20°-25°C (68°-77°F)

Inactive ingredients (Day)

corn starch, microcrystalline cellulose, polyethylene glycol, polysorbate 80, polyvinyl alcohol, potassium sorbate, povidone, sodium lauryl sulfate, stearic acid, talc.

Questions or comments? (Day)

call toll-free 1-855-874-0970 (English/Spanish) weekdays

Active ingredients (in each caplet) (Night)

Acetaminophen 500 mg
Chlorpheniramine maleate 2 mg
Phenylephrine hydrochloride 5 mg

Purposes (Night)

Pain reliever/fever reducer
Antihistamine
Nasal decongestant

Uses (Night)

Temporarily relieves common cold/flu symptoms:
• nasal congestion • sneezing • headache
• runny nose • fever • sore throat
• minor aches and pains

Warnings (Night)

Liver warning: This product contains acetaminophen. Severe liver damage may occur if you take:
• more than 4000 mg of acetaminophen in 24 hours, which is the maximum daily amount
• with other drugs containing acetaminophen
• 3 or more alcoholic drinks every day while using this product
Allergy alert: Acetaminophen may cause severe skin reactions. Symptoms may include:
• skin reddening • blisters • rash
If a skin reaction occurs, stop use and seek medical help right away.
Sore throat warning: If sore throat is severe, persists for more than 2 days, occurs with or is followed by fever, headache, rash, nausea, or vomiting, ask a doctor promptly.

Do not use
• with any other drug containing acetaminophen (prescription or nonprescription). If you are not sure whether a drug contains acetaminophen, ask a doctor or pharmacist.
• if you are now taking a prescription monoamine oxidase inhibitor (MAOI) (certain drugs for depression, psychiatric, or emotional conditions, or Parkinson’s disease), or for 2 weeks after stopping the MAOI drug. If you do not know if your prescription drug contains an MAOI, ask a doctor or pharmacist before taking this product.

Ask a doctor before use if you have
• liver disease • heart disease
• diabetes • high blood pressure
• thyroid disease • glaucoma
• trouble urinating due to an enlarged prostate gland
• a breathing problem such as emphysema or chronic bronchitis

Ask a doctor or pharmacist before use if you are
• taking the blood thinning drug warfarin
• taking sedatives or tranquilizers

When using this product
• do not exceed recommended dosage
• drowsiness may occur • avoid alcoholic drinks
• alcohol, sedatives, and tranquilizers may increase drowsiness effect
• be careful when driving a motor vehicle or operating machinery
• excitability may occur, especially in children

Stop use and ask a doctor if
• pain or nasal congestion gets worse or lasts more than 7 days
• fever gets worse or lasts more than 3 days
• redness or swelling is present
• you get nervous, dizzy, or sleepless • new symptoms occur
These could be signs of a serious condition.

PREGNANCY OR BREAST FEEDING

If pregnant or breast-feeding, ask a health professional before use.

Keep out of reach of children.

Overdose warning: In case of overdose, get medical help or contact a Poison Control Center right away (1-800-222-1222).
Quick medical attention is critical for adults as well as for children even if you do not notice any signs or symptoms.

Directions (Night)

• do not take more than directed (see overdose warning).
• adults and children 12 years of age and over: take 2 caplets every 6 hours as needed.
• do not take more than 8 caplets in 24 hours.
• children under 12 years of age: ask a doctor.

Other information (Night)

store at 20°-25°C (68°-77°F)

Inactive ingredients (Night)

corn starch, D&C yellow No. 10 aluminum lake, FD&C yellow No. 6 aluminum lake, microcrystalline cellulose, polyethylene glycol,
polyvinyl alcohol, potassium sorbate, povidone, sodium lauryl sulfate, stearic acid, talc, titanium dioxide.

Questions or comments? (Night)

call toll-free 1-855-874-0970 (English/Spanish) M - F, 8am -5pm EST

NDC 71179-025-28

CONTAC®

COLD + FLU

DAY

Acetaminophen -

Pain reliever/Fever reducer

Phenylephrine hydrochloride -

Nasal decongestant

Head & Body Aches

Fever • Sore Throat

Nasal Congestion

Sinus Pressure

16 CAPLETS

NIGHT

Acetaminophen -

Pain reliever/Fever reducer

Chlorpheniramine maleate -

Antihistamine

Phenylephrine hydrochloride -

Nasal decongestant

Head & Body Aches

Fever • Sore Throat

Nasal Congestion

Sinus Pressure

Runny Nose • Sneezing

12 CAPLETS

Maximum Strength

Multi-Symptom

DISTRIBUTED BY:

Vespyr Brands®, Inc.

East Windsor NJ 08520

©2022 Vespyr Brands®, Inc.

All rights reserved

CONTAC® is a registered trademark of Vespyr Brands®, Inc.

www.contac.com

Made in Canada